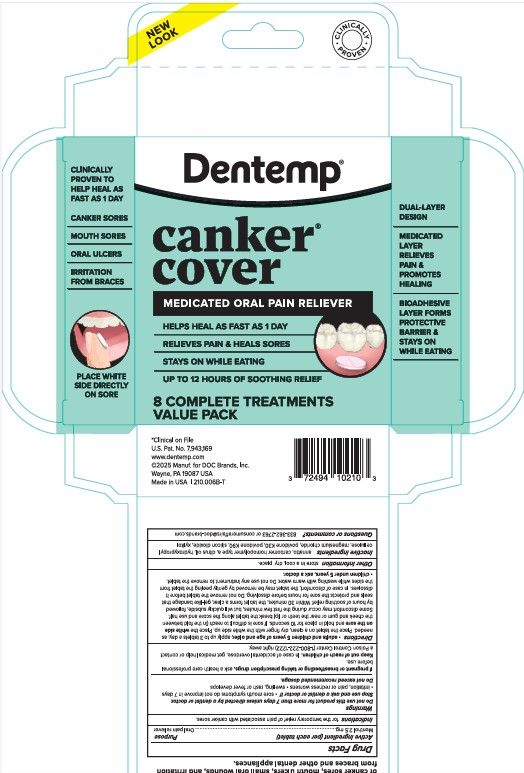 DRUG LABEL: Dentemp Canker Cover
NDC: 73653-210 | Form: TABLET, EXTENDED RELEASE
Manufacturer: DOC Brands
Category: otc | Type: HUMAN OTC DRUG LABEL
Date: 20260108

ACTIVE INGREDIENTS: MENTHOL 2.5 mg/1 1
INACTIVE INGREDIENTS: MAGNESIUM CHLORIDE; SILICON DIOXIDE; ANNATTO; CARBOMER HOMOPOLYMER TYPE A; CITRUS LIMON FRUIT OIL; HYDROXYPROPYL CELLULOSE, UNSPECIFIED; POVIDONE K30; POVIDONE K90; XYLITOL

Dentemp Canker Cover 8ct

Active Ingredient (per each tablet)

Menthol 2.5 mg

Purpose

Ora pain reliever

Indications

for the temporary relief of pain associated with Canker Sores

Warnings

Do not use this product for more than 7 days unless directed by a dentist or doctor. Stop use and ask a dentist or doctor if • sore mouth symptoms do not improve in 7 days • irritation, pain or redness worsens • swelling, rash or fever develops.

Do not exceed recommended dosage.

PREGNANCY OR BREAST FEEDING

If pregnant or breastfeeding or taking prescription drugs, ask a health care professional before use.

Keep out of reach of children. In case of accidental overdose, get medical help or contact a Poison Control Center (1-800-222-1222) right away.

Directions

• adults and children 5 years of age and older, apply up to 3 tablets a day, as needed. Place the tablet on a clean, dry finger with the white side up. Place the white side on the sore and hold in place for 10 seconds. If sore is difficult to reach (in the fold between the cheek and gum or near the teeth or lip) break the tablet along the score and use half. Some discomfort may occur during the first few minutes, but will quickly subside, followed by hours of soothing relief. Within 30 minutes, the tablet forms a clear, gel-like bandage that seals and protects the sore for hours before dissolving. Do not remove the tablet before it dissolves. In case of discomfort, the tablet may be removed by gently peeling the tablet from the sides while washing with warm water. Do not use any instrument to remove the tablet. • children under 5 years, ask a doctor.

Other information

store in a cool, dry place.

Inactive ingredients

annatto, carbomer homopolymer type a, citrus oil, hydroxypropyl cellulose, magnesium chloride, povidone K30, povidone K90, silicon dioxide, xylitol

Questions or comments?

833-362-2763 or consumeraffairs@doc-brands.com